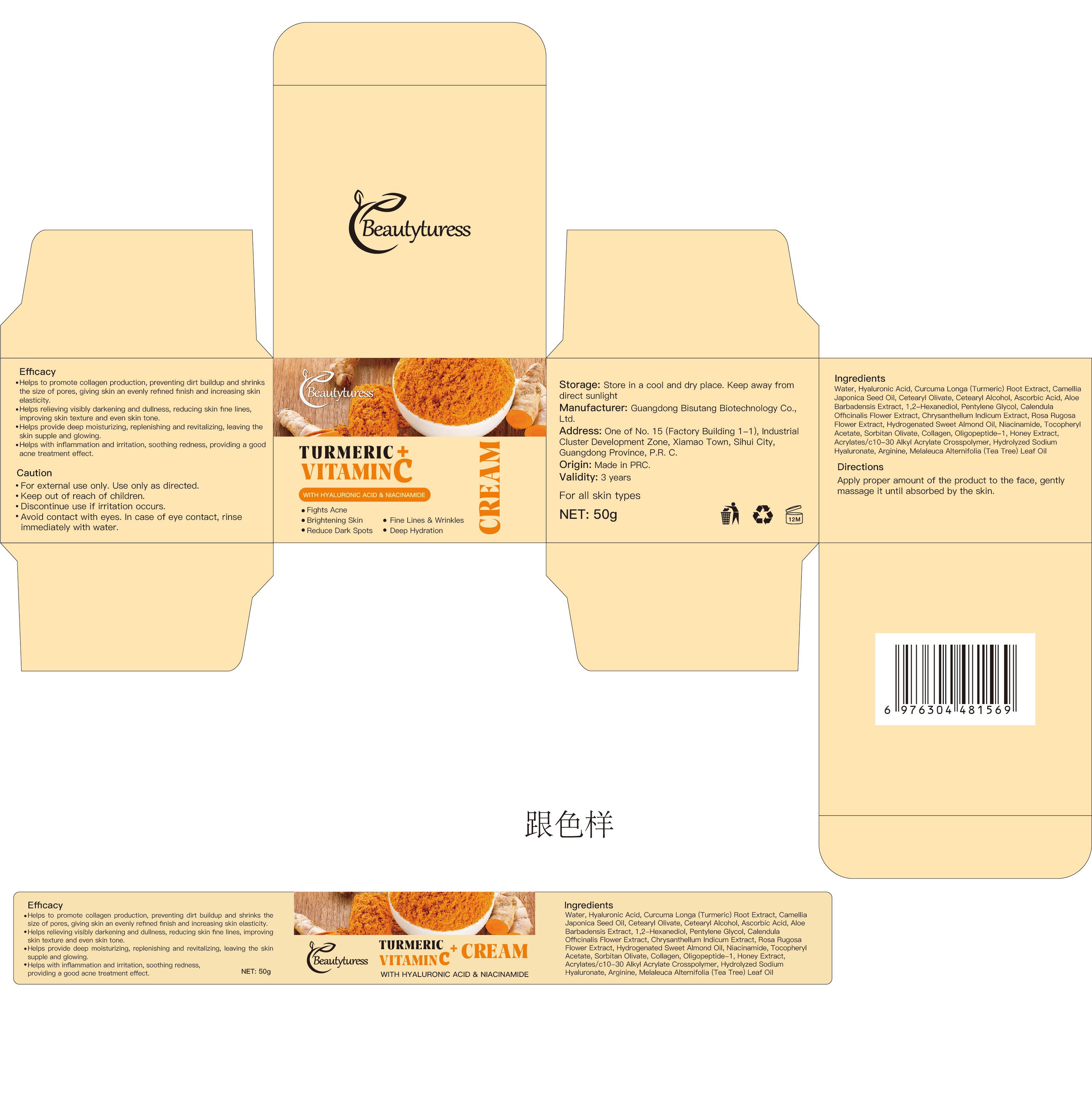 DRUG LABEL: Beautyturess Turmeric Face Cream
NDC: 84753-003 | Form: EMULSION
Manufacturer: Guangdong Bisutang Biotechnology Co., Ltd.
Category: otc | Type: HUMAN OTC DRUG LABEL
Date: 20241009

ACTIVE INGREDIENTS: TETRAHYDROCURCUMIN DIACETATE 0.5 mg/50 g
INACTIVE INGREDIENTS: WATER; PETROLATUM; BUTYLENE GLYCOL; FOLIC ACID; SODIUM CHLORIDE; METHYLPARABEN; PEG-9 DIGLYCIDYL ETHER/SODIUM HYALURONATE CROSSPOLYMER; PHENOXYETHANOL; GLYCERIN; SORBITOL; POLYACRYLAMIDE (10000 MW); SHEA BUTTER; CUPRIC TRIETHANOLAMINE; XANTHAN GUM; MINERAL OIL; CARBOMER 1342; BUTYROSPERMUM PARKII (SHEA) BUTTER UNSAPONIFIABLES; PEG-120 GLYCERYL STEARATE

Active Ingredient

（Tetrahydrocurcumin）：0.001%

PURPOSE

After cleansing andtoning, take an appropriate amount ofthis product and apply it evenly on theface, massage until absorbed

ASK DOCTOR

If you have skin allergies or sensitive skin, consult a doctor before use.

DOSAGE AND ADMINISTRATION

Apply an appropriate amount to the face and neck, gently massage until absorbed. Recommended to use 1-2 times daily for optimal results.

WHEN USING

Avoid contact with eyes and broken skin. If redness or irritation occurs, stop use immediately and consult a doctor.

WARNINGS

For external use only. Avoid contact with wounds or broken skin. If discomfort persists, stop using and consult a doctor.

INDICATIONS AND USAGE

Helps improve skin texture and tone, providing moisturization.

Keep out of reach of children. If swallowed, get medical help or contact a Poison Control Center right away.
Tenir hors de portée des enfants
En cas d'ingestion, consulter un médecin ou appeler un centre antipoison immédiatement.

INACTIVE INGREDIENT

Aloe Barbadensis Leaf Juice, C12-15 Alky Benzoate, Caprylic/Capric Triglyceride, Glyceryi Stearate, Helianthus Annuus(Sunflower) Seed Oil, Ricinus Communis (Castor) Seed Oil, Beeswax, Oryza Sativa (Rice) Bran Wax, Sorbitan Sesquioleate，glycerin, Cetyi Alcohol, Stearyl Alcohol, Magnesium Aluminum silicate, Butyrospermum Parki (Shea) Butter, Camellia Sinensis flower extract, Ilex Paraguariensis Leaf Extract, Rosa Canina Fruitoil, Tocopheryi Acetate, Carthamus Tinctorius (Safflower) Seed, Oilrubus Idaeus (Raspberry) Fruit Extract, Squalane, Xanthan Gum, Propanediol, Ethylhexy glycerin, Potassium Sorbate, Fragrance